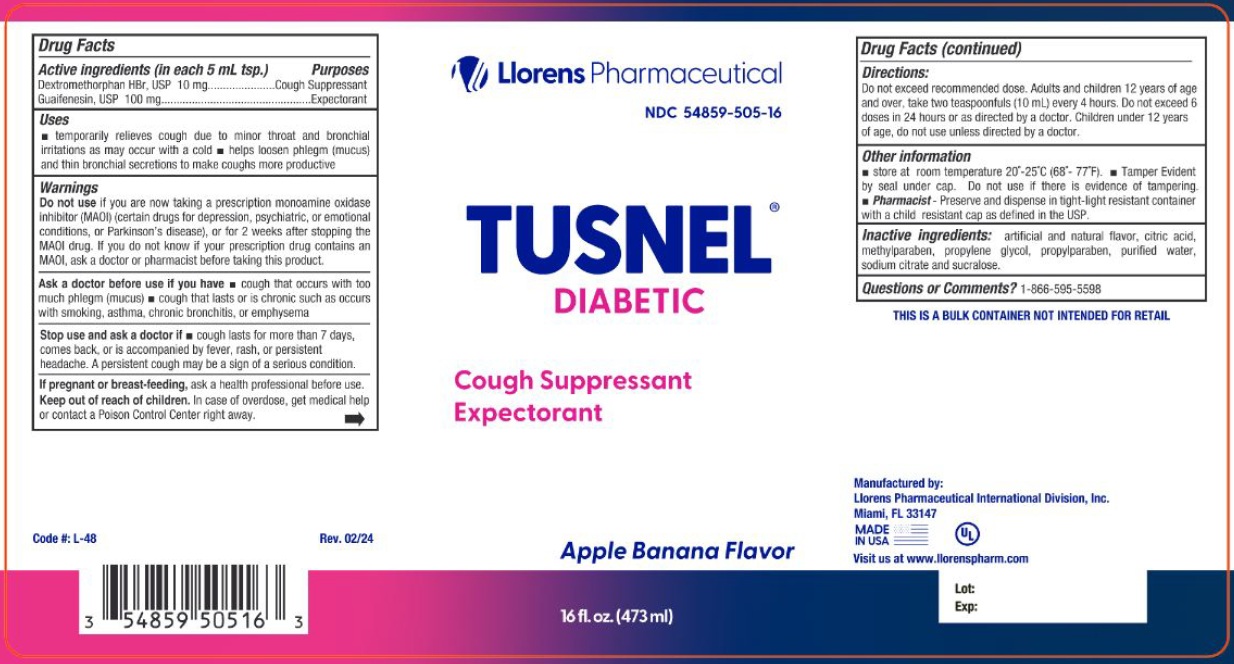 DRUG LABEL: Tusnel Diabetic
NDC: 54859-505 | Form: LIQUID
Manufacturer: LLORENS PHARMACEUTICALS INTERNATIONAL DIVISION
Category: otc | Type: HUMAN OTC DRUG LABEL
Date: 20251229

ACTIVE INGREDIENTS: DEXTROMETHORPHAN HYDROBROMIDE 10 mg/5 mL; GUAIFENESIN 100 mg/5 mL
INACTIVE INGREDIENTS: SUCRALOSE; CITRIC ACID MONOHYDRATE; METHYLPARABEN; PROPYLENE GLYCOL; PROPYLPARABEN; WATER; SODIUM CITRATE

Llorens-TusnelDiabetic 505

Active Ingredients (in each 5 mL tsp.) Purpose

Dextromethorphan HBr USP........ 10 mg ................................. Cough Suppressant

Guaifenesin USP ............. 100 mg ......................................... Expectorant

Purpose

Cough Suppressant

Expectorant

Warnings

Do not useif you are now taking a prescription monoamine oxidase inhibitor (MAOI) (certain drugs for depression, psychiatric, or emotional conditions, or Parkinson's disease), or if 2 weeks after stopping the MAOI drug. If you do not know if your prescription drug contains an MAOI, ask a doctor or pharmacist before giving this product.

Ask a doctor before use if you have

- a cough that occurs with too much phlegm (mucus)
- cough that lasts or is chronic such as occurs with smoking, asthma, chronic bronchitis, or emphysema

Stop use and ask a doctor if cough last more than 7 days, comes back, or is accompanied by fever, rash or persistent headache. A persistent cough could b a sign of a serious condition.

KEEP OUT OF REACH OF CHILDREN

Keep out of the reach of children.In case of overdose, get medical help or contact a Poison Center right away.

PREGNANCY OR BREAST FEEDING

If pregnant or breast-feeding,ask a health professional before use.

Directions

Do not exceed more than 6 doses in any 24-hour period or as directed by a doctor.

Age | Dose
Adults and children 12 years of age and over | 2 teaspoonfuls (10 mL) every 4 hours
Under 2 years of age | Do not use

Uses
Temporarily relieves cough due to minor throat and bronchial irritation as may occur with a cold
Helps loosen phlegm (mucus) and thin bronchial secretions to make coughs more productive

INACTIVE INGREDIENT

Inactive Ingredients: anhydrous citric acid, flavor, methylparaben, propylene glycol, propylparaben, purified water, sodium citrate dihydrate and sucralose.

Questions or Comments?1-866-595-5598

Distributed By: Llorens International Division, Miami FL 33165